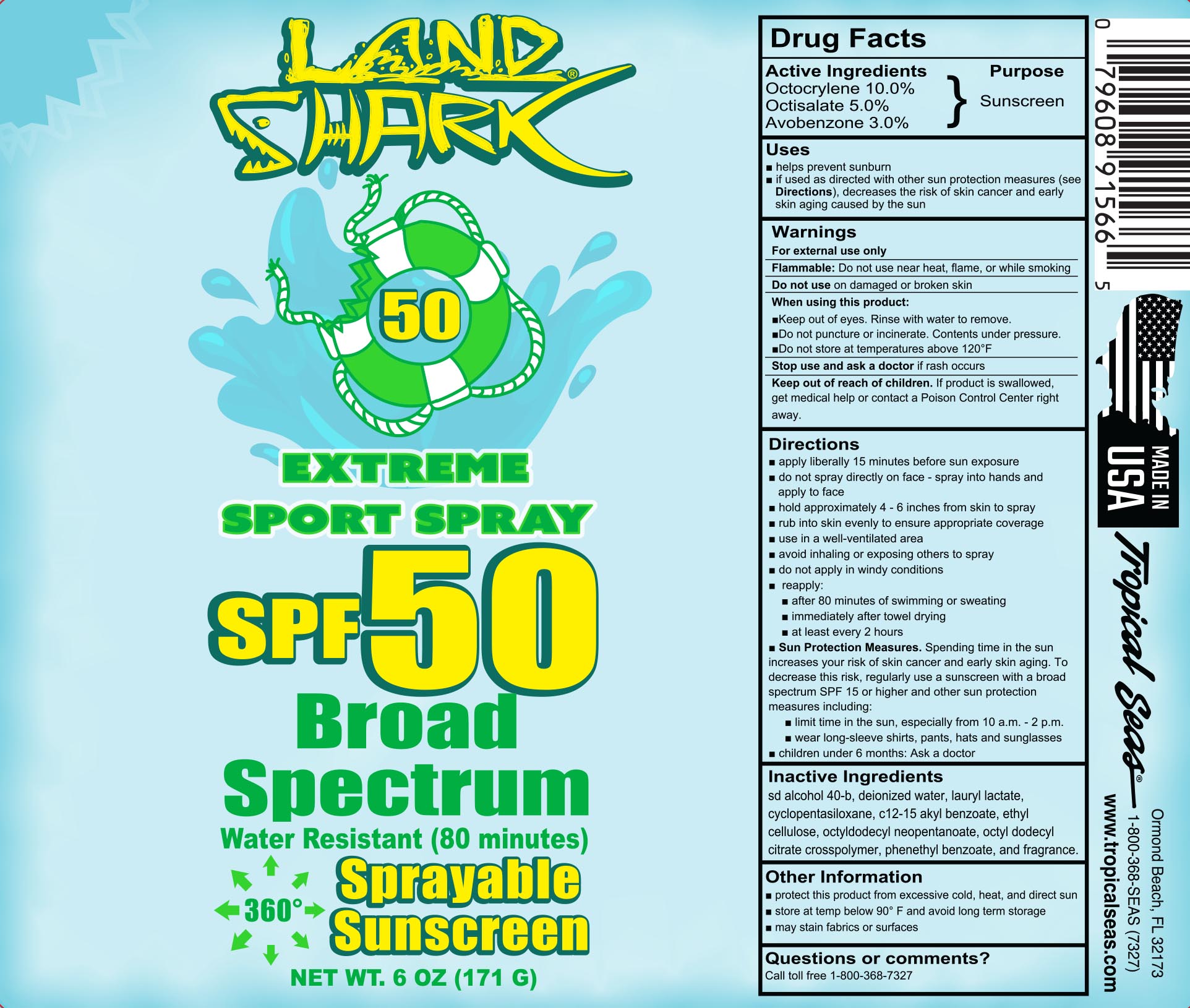 DRUG LABEL: Land Shark SPF 50 Sport
NDC: 52854-956 | Form: SPRAY
Manufacturer: Tropical Seas, Inc.
Category: otc | Type: HUMAN OTC DRUG LABEL
Date: 20251104

ACTIVE INGREDIENTS: OCTOCRYLENE 10 g/100 mL; OCTISALATE 5 g/100 mL; AVOBENZONE 3 g/100 mL
INACTIVE INGREDIENTS: PHENETHYL BENZOATE; CYCLOMETHICONE 5; LAURYL LACTATE; ACRYLATE/ISOBUTYL METHACRYLATE/N-TERT-OCTYLACRYLAMIDE COPOLYMER (75000 MW); OCTYLDODECYL CITRATE CROSSPOLYMER; ALCOHOL; OCTYLDODECYL NEOPENTANOATE; ALKYL (C12-15) BENZOATE

Land Shark SPF 50 Sport Spray

Drug Facts

Active Ingredients

Octocrylene 10.0%

Octisalate 5.0%

Avobenzone 3.0%

Purpose

Sunscreen

Uses

- helps prevent sunburn
- if used as directed with other sun protection measures (see Directions), decreases the risk of skin cancer and early skin aging caused by the sun

Warnings

For external use only

Flammable: Do not use near heat, flame, or while smoking

Do not use on damaged or broken skin

When using this product:

- Keep out of eyes. Rinse with water to remove.
- Do not puncture or incinerate. Contents under pressure.
- Do not store at temperatures above 120° F

Stop use and ask a doctor if rash occurs

Keep out of reach of children. If product is swallowed, get medical help or contact a Poison Control Center right away.

Directions

- apply liberally 15 minutes before sun exposure
- do not spray directly on face - spray into hands and apply to face
- hold approximately 4 - 6 inches from skin to spray
- rub into skin evenly to ensure appropriate coverage
- use in a well-ventilated area
- avoid inhaling or exposing others to spray
- do not apply in windy conditions
- reapply:
  - after 80 minutes of swimming or sweating
  - immediately after towel drying
  - at least every 2 hours
- Sun Protection Measures. Spending time in the sun increases your risk of skin cancer and early skin aging. To decrease this risk, regularly use a sunscreen with a broad spectrum SPF 15 or higher and other sun protection measures including:
  - limit time in the sun, especially from 10 a.m. - 2 p.m.
  - wear long-sleeve shirts, pants, hats and sunglasses
- children under 6 months: Ask a doctor

Inactive Ingredients

sd alcohol 40-b, deionized water, lauryl lactate, cyclopentasiloxane, c12-15 alcohols benzoate, acrylates octylacrylamide copolymer, octyldodecyl neopentanoate, octyl dodecyl citrate crosspolymer, phenethyl benzoate, and fragrance.

Other Information

- protect this product from excessive cold, heat, and direct sun.
- store at temp below 90º F and avoid long term storage
- may stain fabrics or surfaces

Questions or comments?

Call toll free 1-800-368-7327

Principal Display Panel - Bottle Label

180ml NDC 52854-956-01